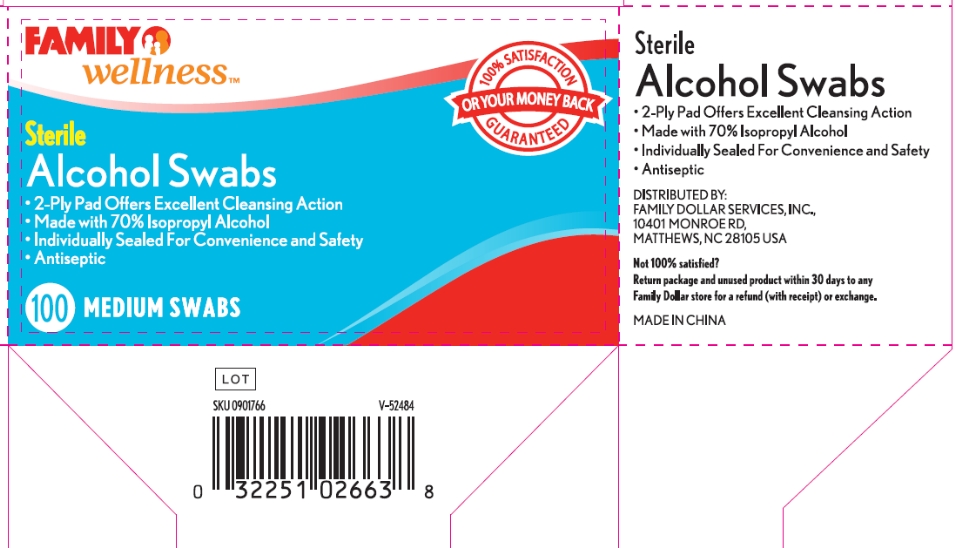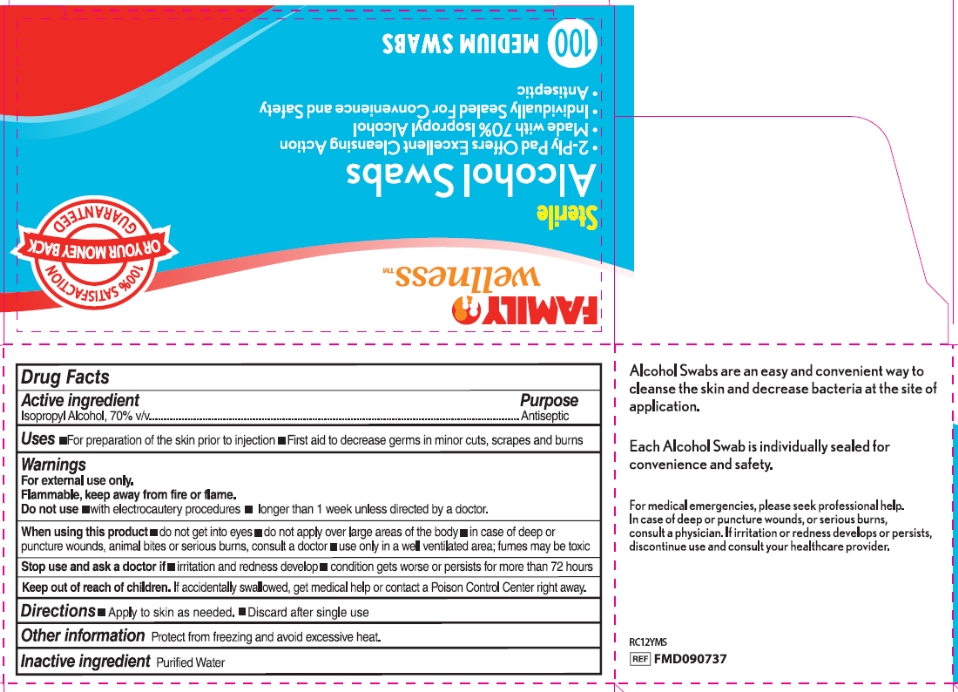 DRUG LABEL: Family Wellness Sterile Alcohol
NDC: 55319-805 | Form: SWAB
Manufacturer: Family Dollar Services Inc
Category: otc | Type: HUMAN OTC DRUG LABEL
Date: 20120427

ACTIVE INGREDIENTS: ISOPROPYL ALCOHOL 70 mL/100 mL
INACTIVE INGREDIENTS: WATER

Drug Facts

Active ingredient

Isopropyl alcohol, 70% v/v

Purpose

Antiseptic

Uses

- For preparation of the skin prior to injection
- First aid to decrease germs in minor cuts, scrapes and burns

Warnings

For external use only.

Flammable, keep away from fire or flame.

Do not use

- with electrocautery procedures
- longer than 1 week unless directed by a doctor

When using this product

- do not get into eyes
- do not apply over large areas of the body
- in case of deep or puncture wounds, animal bites or serious wounds, consult a doctor
- use only in a well ventilated area; fumes may be toxic

Stop use and ask a doctor if

- irritation and redness develop
- condition gets worse or persists for more than 72 hours

Keep out of reach of children.

If swallowed, get medical help or contact a Poison Control Center right away.

Directions

- Apply to skin as needed.
- Discard after single use

Other information

Protect from freezing and avoid excessive heat.

Inactive ingredients

purified water

Package/Label Principal Display Panel

Family Wellness

Sterile Alcohol Swabs

- 2-Ply Pad Offers Excellent Cleansing Action
- Made with 70% Isopropyl Alcohol
- Individually Sealed For Convenience and Safety
- Antiseptic

100 MEDIUM SWABS